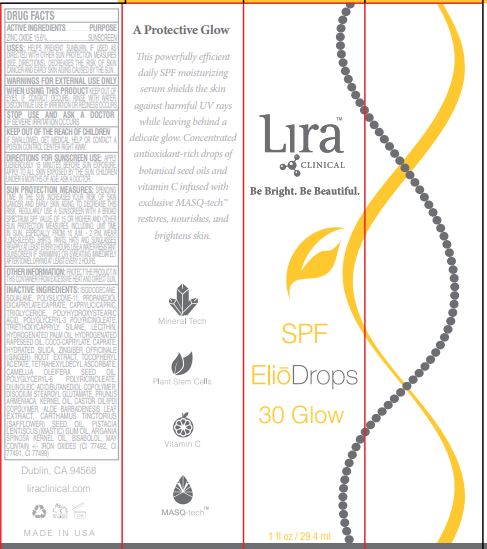 DRUG LABEL: SPF Elio Drops 30 Glow
NDC: 62742-4233 | Form: CREAM
Manufacturer: Allure Labs Inc
Category: otc | Type: HUMAN OTC DRUG LABEL
Date: 20231028

ACTIVE INGREDIENTS: ZINC OXIDE 15.6 g/100 g
INACTIVE INGREDIENTS: POLYGLYCERIN-3; HYDROGENATED RAPESEED OIL; DISODIUM STEAROYL GLUTAMATE; FERRIC OXIDE RED; FERROSOFERRIC OXIDE; COCO-CAPRYLATE; .ALPHA.-TOCOPHEROL ACETATE; SQUALANE; DIMETHICONE/VINYL DIMETHICONE CROSSPOLYMER (SOFT PARTICLE); HYDROGENATED PALM OIL; SILANE; ALOE VERA LEAF; SAFFLOWER OIL; CAPRYLIC/CAPRIC/LAURIC TRIGLYCERIDE; TRIETHOXYCAPRYLYLSILANE; DILINOLEIC ACID/BUTANEDIOL COPOLYMER; ISODODECANE; CAMELLIA OIL; APRICOT KERNEL OIL; CASTOR OIL; ARGAN OIL; PISTACIA LENTISCUS RESIN OIL; PROPANEDIOL DICAPRYLATE/CAPRATE; POLYHYDROXYSTEARIC ACID (2300 MW); POLYGLYCERYL-3 PENTARICINOLEATE; RED BREAST CICHLID; TETRAHEXYLDECYL ASCORBATE; POLYGLYCERYL-6 POLYRICINOLEATE; FERRIC OXIDE YELLOW; LECITHIN, SOYBEAN; HYDRATED SILICA; GINGER; LEVOMENOL

Drug Facts

ACTIVE INGREDIENTS...………... ZINC OXIDE 15.6%

PURPOSE........................SUNSCREEN

INDICATIONS AND USAGE

USES: HELPS PREVENT SUNBURN. IF USED AS DIRECTED WITH OTHER SUN PROTECTION MEASURES (SEE DIRECTIONS), DECREASES THE RISK OF SKIN CANCER AND EARLY SKIN AGING CAUSED BY THE SUN.

WARNINGS FOR EXTERNAL USE ONLY

DISCONTINUE USE IF IRRITATION OR REDNESS OCCURS.

WHEN USING THIS PRODUCT KEEP OUT OF EYES. IF CONTACT OCCURS, RINSE WITH WATER.

STOP USE AND ASK A DOCTOR IF SEVERE IRRITATION OCCURS.

KEEP OUT OF REACH OF CHILDREN

KEEP OUT OF THE REACH OF CHILDREN IF SWALLOWED, GET MEDICAL HELP OR CONTACT A POISON CONTROL CENTER RIGHT AWAY.

DOSAGE AND ADMINISTRATION

DIRECTIONS FOR SUNSCREEN USE: APPLY GENEROUSLY 15 MINUTES BEFORE SUN EXPOSURE. APPLY TO ALL SKIN EXPOSED BY THE SUN. CHILDREN UNDER 6 MONTHS OF AGE: ASK A DOCTOR

SUN PROTECTION MEASURES: SPENDING TIME IN THE SUN INCREASES YOUR RISK OF SKIN CANCER AND EARLY SKIN AGING. TO DECREASE THIS RISK, REGULARLY USE A SUNSCREEN WITH A BROAD SPECTRUM SPF VALUE OF 15 OR HIGHER AND OTHER SUN PROTECTION MEASURES INCLUDING: LIMIT TIME IN SUN, ESPECIALLY FROM 10 A.M. - 2 P.M. WEAR LONG-SLEEVED SHIRTS, PANTS, HATS AND SUNGLASSES. REAPPLY AT LEAST EVERY 2 HOURS. USE A WATER RESISTANT SUNSCREEN IF SWIMMING OR SWEATING IMMEDIATELY AFTER TOWEL DRYING AT LEAST EVERY 2 HOURS.

OTHER INFORMATION:PROTECT THE PRODUCT IN THIS CONTAINER FROM EXCESSIVE HEAT AND DIRECT SUN.

INACTIVE INGREDIENT

INACTIVE INGREDIENTS:ISODODECANE, SQUALANE, POLYSILICONE-11, PROPANEDIOL DICAPRYLATE/CAPRATE, CAPRYLIC/CAPRIC, TRIGLYCERIDE, POLYHYDROXYSTEARIC ACID, POLYGLYCERYL-3 POLYRICINOLEATE, TRIETHOXYCAPRYLY, SILANE, LECITHIN, HYDROGENATED PALM OIL, HYDROGENATED RAPESEED OIL, COCO-CAPRYLATE, CAPRATE, HYDRATED SILICA, ZINGIBER OFFICINALE (GINGER) ROOT EXTRACT, TOCOPHERYL ACETATE, TETRAHEXYLDECYL ASCORBATE, CAMELLIA OLEIFERA SEED OIL, POLYGLYCERYL-6 POLYRICINOLEATE, DILINOLEIC ACID/BUTANEDIOL COPOLYMER, DISODIUM STEAROYL GLUTAMATE, PRUNUS ARMENIACA, KERNEL OIL, CASTOR OIL/IPDI COPOLYMER, ALOE BARBADENESIS LEAF EXTRACT, CARTHAMUS TINCTORIUS (SAFFLOWER) SEED OIL, PISTACIA LENTISCUS (MASTIC) GUM OIL, ARGANIA SPINOSA KERNEL OIL, BISABOLOL, MAY CONTAIN +/- IRON OXIDES (CI 77492, CI 77491, CI 77499